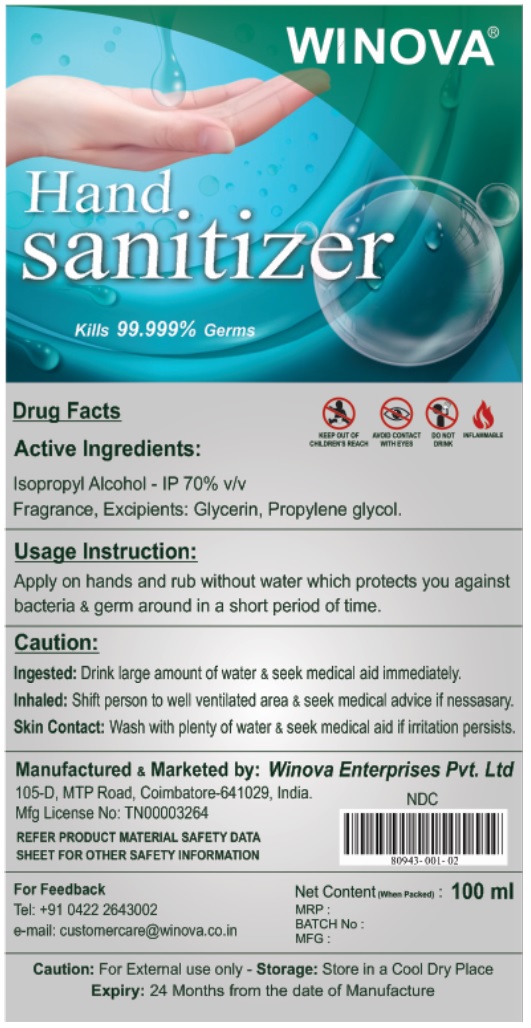 DRUG LABEL: Winova Hand Sanitizer
NDC: 80943-001 | Form: SOLUTION
Manufacturer: WINOVA ENTERPRISES PRIVATE LIMITED
Category: otc | Type: HUMAN OTC DRUG LABEL
Date: 20201105

ACTIVE INGREDIENTS: ISOPROPYL ALCOHOL 70 mL/100 mL
INACTIVE INGREDIENTS: GLYCERIN; PROPYLENE GLYCOL

WINOVA® Hand Sanitizer

Active Ingredients:

Isopropyl Alcohol - IP 70% v/v

Purpose:

Antibacterial

Uses:

Hand sanitizer to kills bacteria & germ around in a short period of time.

Caution:

For External use only

Ingested: Drink large amount of water & seek medical aid immediately.

Inhaled: Shift person to well ventilated area & seek medical advice if necessary.

Skin Contact: Wash with plenty of water & seek medical aid if irritation persists.

KEEP OUT OF CHILDREN'S REACH

Usage Instruction:

Apply on hands and rub without water which protects you against bacteria & germ around in a short period of time.

Storage:

Store in a Cool Dry Place

Inactive Ingredients:

Glycerin, Propylene glycol, Fragrance

Kills 99.999% Germs

AVOID CONTACT WITH EYES

DO NOT DRINK

INFLAMMABLE

Manufactured & Marketed by: Winova Enterprises Pvt. Ltd

105-D, MTP Road, Coimbatore- 641029, India.

Mfg License No: TN00003264

REFER PRODUCT MATERIAL SAFETY DATA SHEET FOR OTHER SAFETY INFORMATION

For Feedback

Tel: +91 0422 2643002

e-mail: customercare@winova.co.in

Expiry: 24 Months from the date of Manufacture